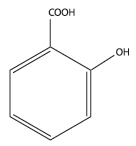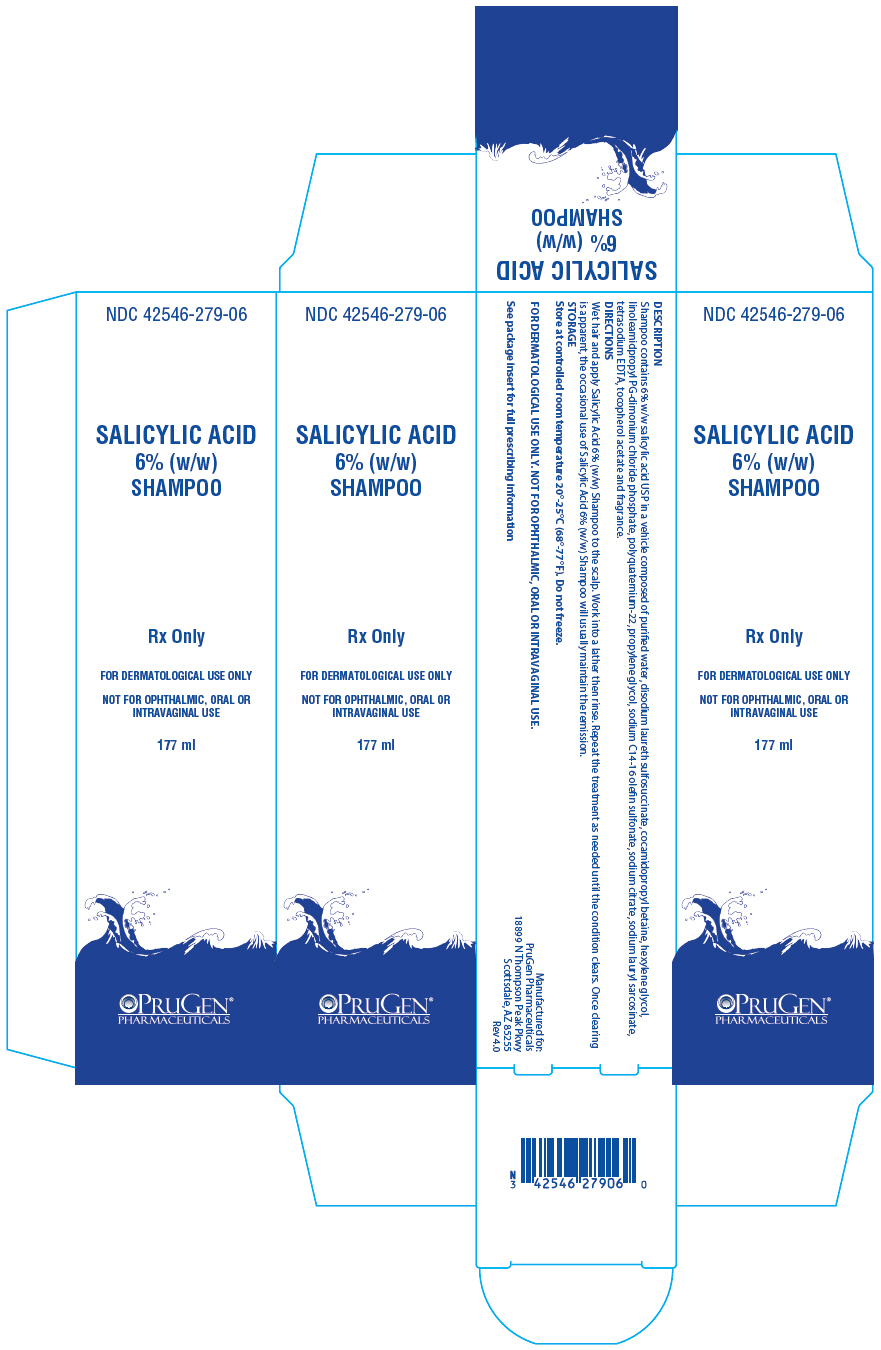 DRUG LABEL: Salicylic Acid 6 percent
NDC: 42546-279 | Form: SHAMPOO
Manufacturer: PruGen LLC
Category: prescription | Type: HUMAN PRESCRIPTION DRUG LABEL
Date: 20220202

ACTIVE INGREDIENTS: salicylic acid 6 mg/100 mL
INACTIVE INGREDIENTS: water; CARBOMER COPOLYMER TYPE A (ALLYL PENTAERYTHRITOL CROSSLINKED); SODIUM LAURETH-3 SULFATE; TROLAMINE; QUATERNIUM-22; COCAMIDOPROPYL BETAINE; BEHENTRIMONIUM METHOSULFATE; PROPYLPARABEN; METHYLPARABEN; GLYCERIN; EDETATE DISODIUM; CHAMOMILE

Salicylic Acid 6% (w/w) Shampoo

Rx Only

FOR DERMATOLOGICAL USE ONLY. NOT FOR OPHTHALMIC,ORAL OR INTRAVAGINAL USE.

DESCRIPTION

SHAMPOO contains 6% w/w salicylic acid USP in a vehicle composed of purified water, disodium laureth sulfosuccinate, cocamidopropyl betaine, hexylene glycol, linoleamidpropyl PG-dimonium chloride phosphate, polyquaternium-22, propylene glycol, sodium C14-16 olefin sulfonate, sodium citrate, sodium lauryl sarcosinate, tetrasodium EDTA, tocopherol acetate and fragrance.

Salicylic acid is the 2-hydroxy derivative of benzoic acid having the following structure:

CLINICAL PHARMACOLOGY

Salicylic acid has been shown to produce desquamation of the horny layer of skin while not effecting qualitative or quantitative changes in the structure of the viable epidermis. The mechanism of action has been attributed to a dissolution of inter cellular cement substance.

In a study of the percutaneous absorption of salicylic acid in a 6%salicylic acid gel in four patients with extensive active psoriasis, Taylor and Halprin showed that the peak serum salicylate levels never exceeded 5 mg/100 ml even though more than 60% of the applied salicylic acid was absorbed. Systemic toxic reactions are usually associated with much higher serum levels (30 to 40 mg/100 ml).

Peak serum levels occurred within five hours of the topical application under occlusion. The sites were occluded for 10 hours over the entire body surface below the neck. Since salicylates are distributed in the extra cellular space, patients with a contracted extra cellular space due to dehydration or diuretics have a higher salicylate levels than those with a normal extra cellular space. (See PRECAUTIONS)

The major metabolites identified in the urine after topical administration are salicyluric acid (52%), salicylate glucuronides (42%) and free salicylic acid (6%). The urinary metabolites after percutaneous absorption differ from those after oral salicylate administration; those derived from percutaneous absorption contain more salicylate glucuronides and less salicyluric and salicylic acid. Almost 95% of a single dose of salicylate is excreted within 24 hours of its entrance into the extracellular space.

Fifty to eighty percent of a salicylate is protein bound to albumin. Salicylates compete with the binding of several drugs and can modify the actions of these drugs; by similar competitive mechanisms other drugs can influence the serum levels of salicylate.(See PRECAUTIONS)

INDICATIONS AND USAGE

For Dermatologic Use

Salicylic Acid 6% (w/w) Shampoo is a topical aid in the removal of excessive keratin in hyperkeratotic skin disorders, including verrucae, and the various ichthyoses (vulgaris, sex-linked and lamellar), keratosis palmaris and plantaris, keratosis pilaris, pityriasis rubra pilaris, and psoriasis (including body, scalp, palms and soles).

For Podiatric Use

Salicylic Acid 6% (w/w) Shampoo is a topical aid in the removal of excessive keratin on the dorsal and plantar hyperkeratotic lesions. Topical preparations of 6% salicylic acid have been reported to be useful adjunctive therapy for verrucae plantares.

CONTRAINDICATIONS

Salicylic Acid 6% (w/w) Shampoo should not be used in any Patient known to be sensitive to salicylic acid or any other listed ingredients. Salicylic Acid 6% (w/w) Shampoo should not be used in children under 2 years of age.

WARNINGS

Prolonged use over large areas, especially in children and those patients with significant renal or hepatic impairment could resultin salicylism. Excessive application of the product other than is needed to cover the affected area will not result in more therapeutic benefit. Concomitant use of other drugs which may contribute to elevated serum salicylate levels should be avoided where the potential for toxicity is present. In children under 12 years of age and those patients with renal or hepatic impairment, the area to be treated should be limited and the patient monitored closely for signs of salicylate toxicity: nausea, vomiting, dizziness, loss of hearing, tinnitus, lethargy, hyperpnea, diarrhea, and psychic disturbances. In the event of salicylic acid toxicity, the use of the Salicylic Acid 6% (w/w) Shampoo should be discontinued. Fluids should be administered to promote urinary excretion. Treatment with sodium bicarbonate (oral or intravenous) should be instituted as appropriate. Patients should be cautioned against the use of oral aspirin and other salicylate containing medications, such as sports and injury creams, to avoid additional excessive exposure to salicylic acid. Where needed, aspirin should be replaced by an alternative non-steroidal, anti-inflammatory agent that is not salicylate based.

Due to potential risk of developing Reye's syndrome, salicylate products should not be used in children and teenagers with varicella or influenza, unless directed by a physician.

PRECAUTIONS

For external use only. Avoid contact with eyes and other mucous membranes.

DRUG INTERACTIONS

The following interactions are from a published review and include reports concerning both oral and topical salicylate administration. The relationship of these interactions to the use of Salicylic Acid 6% (w/w) Shampoo is not known.

I.Due to the competition of salicylate with other drugs for binding to serum albumin the following drug interactions may occur:

DRUG | DESCRIPTION OF INTERACTION
Sulfonylureas | Hypoglycemia potentiated.
Methotrexate | Decreases tubular reabsorption; clinical toxicity from methotrexate can result.
Oral Anticoagulants | Increased bleeding.

II.Drugs changing salicylate levels by altering renal tubular reabsorption:

DRUG | DESCRIPTION OF INTERACTION
Corticosteroids | Decreases plasma salicylate level; tapering doses of steroids may promote salicylism.
Acidifying Agents | Increases plasma salicylate level.
Alkanizing Agents | Decreased plasma salicylate levels.

III.Drugs with complicated interactions with salicylates:

DRUG | DESCRIPTION OF INTERACTION
Heparin | Salicylate decreases platelet adhesiveness and interferes with hemostasis in heparin treated patients.
Pyrazinamide | Inhibits pyrazinamide-induced hyperuricemia.
Uricosuric | Effect of probenemide, sulfinpyrazone and phenylbutazone inhibited.

The following alterations of laboratory tests have been reported during salicylate therapy:

LABORATORY TESTS | EFFECT OF SALICYLATES
Thyroid Function | Decreased PBI; increased T3 uptake.
Urinary Sugar | False negative with glucose oxidase; false positive with Clinitest with high-dose salicylate therapy (2-5g q.d.).
5- Hydroxyindole acetic acid | False negative with fluorometric test.
Acetone, ketone bodies | False positive FeCl3 in Gerhardt reaction; red color persists with boiling
.17-OH corticosteroids | False reduced values with >4.8g q.d. salicylate.
Vanilmandelic acid | False reduced values.
Uric acid | May increase or decrease depending ondose.
Prothrombin | Decreased levels; slightly increased prothrombin time.

Pregnancy (Category C)

TERATOGENIC EFFECTS

Salicylic acid has been shown to be teratogenic in rats and monkeys. It is difficult to extrapolate from oral doses of acetylsalicylic acid used in these studies to topical administration as the oral dose to monkeys may represent six times the maximal daily human dose of salicylic acid when applied topically over a large body surface. There are no adequate and well-controlled studies in pregnant women. Salicylic Acid 6% (w/w) Shampoo should be used during pregnancy only if the potential benefit justifies the potential risk to the fetus.

Nursing Mothers

Because of the potential for serious adverse reactions in nursing infants from the mother's use of Salicylic Acid 6% (w/w) Shampoo, a decision should be made whether to discontinue nursing or to discontinue the drug, taking into account the importance of the drug to the mother. If used by nursing mothers, it should not be used on the chest area to avoid the accidental contamination of the child.

Carcinogenesis, Mutagenesis, Impairment of Fertility

No data is available concerning potential carcinogenic or reproductive effects of Salicylic Acid 6% (w/w) Shampoo. Salicylic acid has been shown to lack mutagenic potential in the Ames Salmonella test.

ADVERSE REACTIONS

Excessive erythema and scaling conceivably could result from use on open skin lesions.

OVERDOSAGE

See WARNINGS.

DOSAGE AND ADMINISTRATION

Wet hair and apply Salicylic Acid 6% (w/w) Shampoo to the scalp. Work into a lather then rinse. Repeat the treatment as needed until the condition clears. Once clearing is apparent, the occasional use of Salicylic Acid 6% (w/w) Shampoo will usually maintain the remission.

HOW SUPPLIED

Salicylic Acid 6% (w/w) Shampoo is available in 177mL plastic bottles (NDC 42546-279-06).

STORAGE AND HANDLING

Store at controlled room temperature 20°-25°C (68°-77°F). Do not freeze.

Manufactured for:
PruGen Pharmaceuticals
18899 N Thompson Peak Pkwy
Scottsdale, AZ 85255
Rev 4.0

PRINCIPAL DISPLAY PANEL - 177 ml Bottle Box

NDC 42546-279-06

SALICYLIC ACID
6% (w/w)
SHAMPOO

Rx Only

FOR DERMATOLOGICAL USE ONLY

NOT FOR OPHTHALMIC, ORAL OR
INTRAVAGINAL USE

177 ml

PRUGEN®
PHARMACEUTICALS